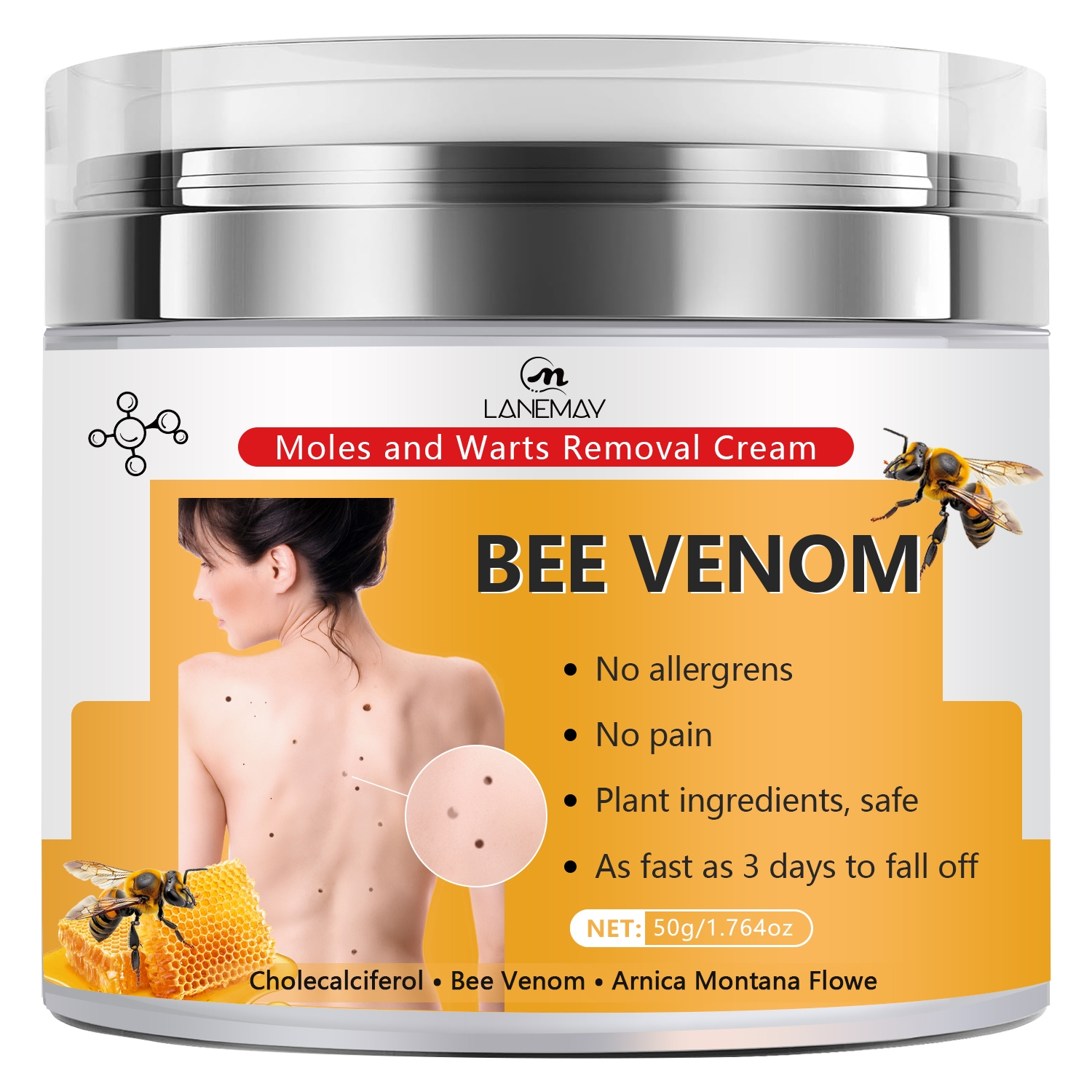 DRUG LABEL: Bee Venom Cream
NDC: 84025-198 | Form: CREAM
Manufacturer: Guangzhou Yanxi Biotechnology Co., Ltd
Category: otc | Type: HUMAN OTC DRUG LABEL
Date: 20241008

ACTIVE INGREDIENTS: MINERAL OIL 3 mg/50 g; GLYCERIN 2 mg/50 g
INACTIVE INGREDIENTS: WATER

DOSAGE AND ADMINISTRATION

First wash and dry the area to be applied.Then simply apply gently to the skin,massage completely and absorb.

WARNINGS

keep out of children

INACTIVE INGREDIENT

Aqua

INDICATIONS AND USAGE

For skin repairing

keep out of children

PURPOSE

skin repairing and brightens skin tone